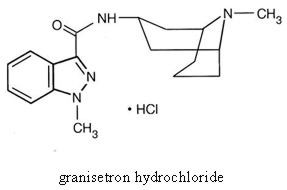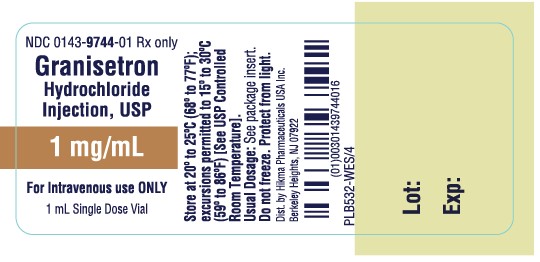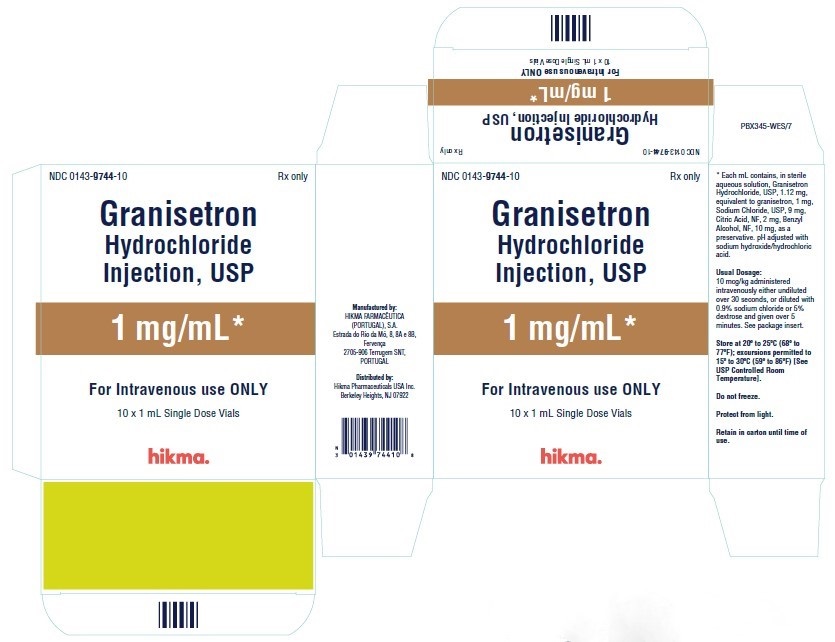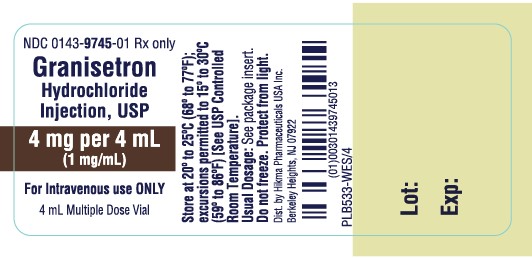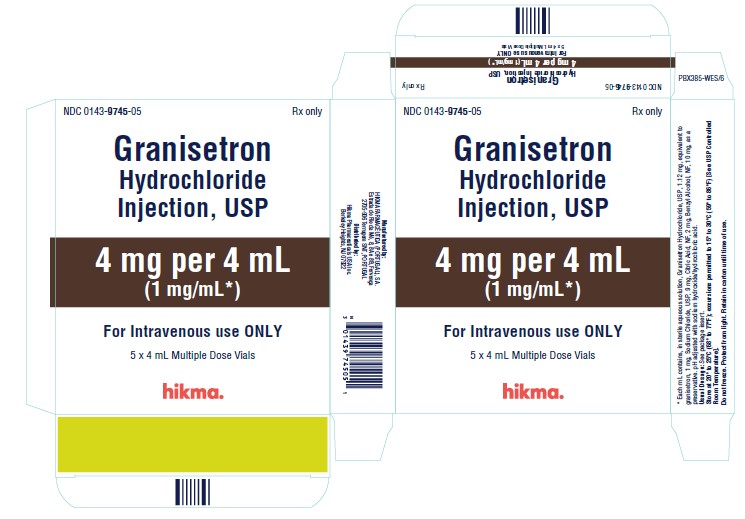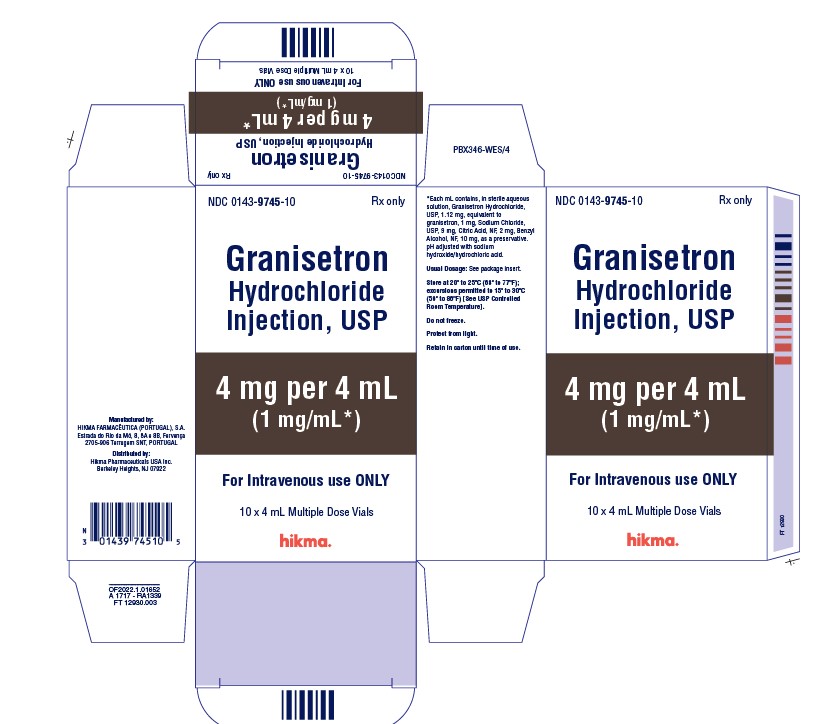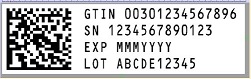 DRUG LABEL: Granisetron Hydrochloride
NDC: 0143-9744 | Form: INJECTION
Manufacturer: Hikma Pharmaceuticals USA Inc.
Category: prescription | Type: HUMAN PRESCRIPTION DRUG LABEL
Date: 20240104

ACTIVE INGREDIENTS: GRANISETRON HYDROCHLORIDE 1 mg/1 mL
INACTIVE INGREDIENTS: SODIUM CHLORIDE 9 mg/1 mL; ANHYDROUS CITRIC ACID 2 mg/1 mL; BENZYL ALCOHOL 10 mg/1 mL; SODIUM HYDROXIDE; HYDROCHLORIC ACID; WATER

HIGHLIGHTS OF PRESCRIBING INFORMATION

These highlights do not include all the information needed to use Granisetron Hydrochloride Injection, USP safely and effectively. See full prescribing information for Granisetron Hydrochloride Injection, USP.
GRANISETRON hydrochloride injection, USP for intravenous use
Initial U.S. Approval: 1993

1 INDICATIONS AND USAGE

Granisetron Hydrochloride Injection, USP is a serotonin-3 (5-HT3) receptor antagonist indicated for:

- Prevention of nausea and/or vomiting associated with initial and repeat courses of emetogenic cancer therapy, including high-dose cisplatin. (1)

2 DOSAGE AND ADMINISTRATION

Prevention of chemotherapy-induced nausea and vomiting (2.1):

- Recommended dosage is 10 mcg/kg intravenously within 30 minutes before initiation of chemotherapy
- Pediatric patients (2 to 16 years): Recommended dosage is 10 mcg/kg

3 DOSAGE FORMS AND STRENGTHS

- Injection 1 mg/mL (free base). (3)

4 CONTRAINDICATIONS

- Hypersensitivity to granisetron or to any of its components. (4)

5 WARNINGS AND PRECAUTIONS

- Granisetron hydrochloride does not stimulate gastric or intestinal peristalsis and should not be used instead of nasogastric suction. (5.1)
- QT prolongation has been reported with granisetron hydrochloride. Use with caution in patients with pre-existing arrhythmias or cardiac conduction disorders. (5.2)
- Hypersensitivity reactions, such as anaphylaxis, shortness of breath, hypotension, and urticaria, may occur in patients with known hypersensitivity to other selective 5-HT3 receptor antagonists. (5.3)
- Contains benzyl alcohol. (5.4)
- Serotonin syndrome has been reported with granisetron products, alone but particularly with concomitant use of serotonergic drugs. (5.5)

6 ADVERSE REACTIONS

Most common adverse reactions:

- Chemotherapy-induced nausea and vomiting (≥3%): Headache, and constipation (6.1)

To report SUSPECTED ADVERSE REACTIONS, contact Hikma Pharmaceuticals USA Inc. at 1-877-845-0689 or FDA at 1-800-FDA-1088 or www. fda.gov/medwatch.

7 DRUG INTERACTIONS

- Granisetron Hydrochloride Injection, USP has been administered safely with benzodiazepines, neuroleptics, and anti-ulcer medications. (7)
- Does not appear to interact with emetogenic cancer chemotherapies. (7)
- Inducers or inhibitors of CYP450 enzymes may change the clearance and therefore the half-life of granisetron. (7)
- Coadministration of granisetron hydrochloride with drugs known to prolong the QT interval and/or are arrhythmogenic may result in clinical consequences. (7)

8 USE IN SPECIFIC POPULATIONS

- Pregnancy: Use only if clearly needed. (8.1)
- Nursing mothers: Caution should be exercised when administered to a nursing woman. (8.3)
- Pediatric use: Safety and efficacy in pediatric patients have not been established for use in postoperative nausea and vomiting. (8.4)
- Geriatric use: No differences in responses between the elderly and younger patients were observed in reported clinical experience. (8.5)

FULL PRESCRIBING INFORMATION

1 INDICATIONS AND USAGE

Granisetron Hydrochloride Injection, USP is a serotonin-3 (5-HT3) receptor antagonist indicated for:

- The prevention of nausea and/or vomiting associated with initial and repeat courses of emetogenic cancer therapy, including high-dose cisplatin.

2 DOSAGE AND ADMINISTRATION

2.1 Prevention of Chemotherapy-Induced Nausea and Vomiting

Adult Patients
The recommended dosage for Granisetron Hydrochloride Injection is 10 mcg/kg administered intravenously within 30 minutes before initiation of chemotherapy, and only on the day(s) chemotherapy is given.

Infusion Preparation
Granisetron Hydrochloride Injection may be administered intravenously either undiluted over 30 seconds or diluted with 0.9% Sodium Chloride or 5% Dextrose and infused over 5 minutes.

Stability
Intravenous infusion of Granisetron Hydrochloride Injection should be prepared at the time of administration. However, Granisetron Hydrochloride Injection has been shown to be stable for at least 24 hours when diluted in 0.9% Sodium Chloride or 5% Dextrose and stored at room temperature under normal lighting conditions.

As a general precaution, Granisetron Hydrochloride Injection should not be mixed in solution with other drugs. Parenteral drug products should be inspected visually for particulate matter and discoloration before administration whenever solution and container permit.

Pediatric Patients
The recommended dose in pediatric patients 2 to 16 years of age is 10 mcg/kg [see Clinical Studies (14)]. Pediatric patients under 2 years of age have not been studied.

3 DOSAGE FORMS AND STRENGTHS

Single Dose Vials for Injection: 1 mg/mL
Multiple Dose Vials for Injection: 4 mg/4 mL (1 mg/mL)

4 CONTRAINDICATIONS

Granisetron Hydrochloride Injection is contraindicated in patients with known hypersensitivity (e.g. anaphylaxis, shortness of breath, hypotension, urticaria) to the drug or to any of its components.

5 WARNINGS AND PRECAUTIONS

5.1 Gastric or Intestinal Peristalsis

Granisetron hydrochloride is not a drug that stimulates gastric or intestinal peristalsis. It should not be used instead of nasogastric suction. The use of granisetron hydrochloride in patients following abdominal surgery or in patients with chemotherapy-induced nausea and vomiting may mask a progressive ileus and/or gastric distention.

5.2 Cardiovascular Events

An adequate QT assessment has not been conducted, but QT prolongation has been reported with granisetron hydrochloride. Therefore, granisetron hydrochloride should be used with caution in patients with pre-existing arrhythmias or cardiac conduction disorders, as this might lead to clinical consequences. Patients with cardiac disease, on cardio-toxic chemotherapy, with concomitant electrolyte abnormalities and/or on concomitant medications that prolong the QT interval are particularly at risk.

5.3 Hypersensitivity Reactions

Hypersensitivity reactions (e.g. anaphylaxis, shortness of breath, hypotension, urticaria) may occur in patients who have exhibited hypersensitivity to other selective 5-HT3 receptor antagonists

5.4 Benzyl Alcohol

Granisetron Hydrochloride Injection 1 mg/mL contains benzyl alcohol. Benzyl alcohol, a component of Granisetron Hydrochloride Injection 1 mg/mL, has been associated with serious adverse reactions and death, particularly in neonates. The “gasping syndrome,” characterized by central nervous system depression, metabolic acidosis, gasping respirations, and high levels of benzyl alcohol and metabolites in blood and urine, has been associated with benzyl alcohol dosages >99 mg/kg/day in neonates and low birth-weight neonates. Additional symptoms may include gradual neurological deterioration, seizures, intracranial hemorrhage, hematologic abnormalities, skin breakdown, hepatic and renal failure, hypotension, bradycardia, and cardiovascular collapse. Although normal therapeutic doses of this product deliver amounts of benzyl alcohol that are substantially lower than those reported in association with the “gasping syndrome,” the minimum amount of benzyl alcohol at which toxicity may occur is not known. Premature and low birth-weight infants, as well as patients receiving high dosages, may be more likely to develop toxicity. Practitioners administering this and other medications containing benzyl alcohol should consider the combined daily metabolic load of benzyl alcohol from all sources.

5.5 Serotonin Syndrome

The development of serotonin syndrome has been reported with 5-HT3 receptor antagonists. Most reports have been associated with concomitant use of serotonergic drugs (e.g., selective serotonin reuptake inhibitors (SSRIs), serotonin and norepinephrine reuptake inhibitors (SNRIs), monoamine oxidase inhibitors, mirtazapine, fentanyl, lithium, tramadol, and intravenous methylene blue). Some of the reported cases were fatal. Serotonin syndrome occurring with overdose of another 5-HT3 receptor antagonist alone has also been reported. The majority of reports of serotonin syndrome related to 5-HT3 receptor antagonist use occurred in a post-anesthesia care unit or an infusion center.

Symptoms associated with serotonin syndrome may include the following combination of signs and symptoms: mental status changes (e.g., agitation, hallucinations, delirium, and coma), autonomic instability (e.g., tachycardia, labile blood pressure, dizziness, diaphoresis, flushing, hyperthermia), neuromuscular symptoms (e.g., tremor, rigidity, myoclonus, hyperreflexia, incoordination), seizures, with or without gastrointestinal symptoms (e.g., nausea, vomiting, diarrhea). Patients should be monitored for the emergence of serotonin syndrome, especially with concomitant use of granisetron and other serotonergic drugs. If symptoms of serotonin syndrome occur, discontinue granisetron and initiate supportive treatment. Patients should be informed of the increased risk of serotonin syndrome, especially if granisetron is used concomitantly with other serotonergic drugs [see Drug Interactions (7), Patient Counseling Information (17)].

6 ADVERSE REACTIONS

QT prolongation has been reported with granisetron hydrochloride [see Warnings and Precautions (5.2) and Drug Interactions (7)].

6.1 Clinical Trials Experience

Because clinical trials are conducted under widely varying conditions, adverse reaction rates observed in the clinical trials of a drug cannot be directly compared to rates in the clinical trials of another drug and may not reflect the rates observed in patients.

Chemotherapy-Induced Nausea and Vomiting
The following have been reported during controlled clinical trials or in the routine management of patients. The percentage figures are based on clinical trial experience only. Table 1 gives the comparative frequencies of the two most commonly reported adverse reactions (≥3%) in patients receiving Granisetron Hydrochloride Injection, in single-day chemotherapy trials. These patients received chemotherapy, primarily cisplatin, and intravenous fluids during the 24-hour period following Granisetron Hydrochloride Injection administration. Reactions were generally recorded over seven days post-Granisetron Hydrochloride Injection administration.

Table 1. Principal Adverse Reactions in Clinical Trials — Single-Day Chemotherapy
Percent of Patients With Reaction
 | Granisetron Hydrochloride Injection 40 mcg/kg (n=1268) | Comparator [Metoclopramide/dexamethasone and phenothiazines/dexamethasone.] (n=422)
Headache | 14% | 6%
Constipation | 3% | 3%

Additional adverse events reported in clinical trials were asthenia, somnolence and diarrhea.

In over 3,000 patients receiving Granisetron Hydrochloride Injection (2 to 160 mcg/kg) in single-day and multiple-day clinical trials with emetogenic cancer therapies, adverse events, other than those adverse reactions listed in Table 1, were observed; attribution of many of these events to granisetron hydrochloride is uncertain.

Hepatic: In comparative trials, mainly with cisplatin regimens, elevations of AST and ALT (>2 times the upper limit of normal) following administration of Granisetron Hydrochloride Injection occurred in 2.8% and 3.3% of patients, respectively. These frequencies were not significantly different from those seen with comparators (AST: 2.1%; ALT: 2.4%).

Cardiovascular: Hypertension (2%); hypotension, arrhythmias such as sinus bradycardia, atrial fibrillation, varying degrees of A-V block, ventricular ectopy including non-sustained tachycardia, and ECG abnormalities have been observed rarely.

Central Nervous System: Agitation, anxiety, CNS stimulation and insomnia were seen in less than 2% of patients. Extrapyramidal syndrome occurred rarely and only in the presence of other drugs associated with this syndrome.

Hypersensitivity: Rare cases of hypersensitivity reactions, sometimes severe (eg, anaphylaxis, shortness of breath, hypotension, urticaria) have been reported.

Other: Fever (3%), taste disorder (2%), skin rashes (1%). In multiple-day comparative studies, fever occurred more frequently with Granisetron Hydrochloride Injection (8.6%) than with comparative drugs (3.4%, P<0.014), which usually included dexamethasone.

6.2 Postmarketing Experience

The following adverse reactions have been identified during post approval use of granisetron hydrochloride. Because these reactions are reported voluntarily from a population of uncertain size, it is not always possible to reliably estimate their frequency or establish a causal relationship to granisetron hydrochloride exposure.

QT prolongation has been reported with granisetron hydrochloride [see Warnings and Precautions (5.2) and Drug Interactions (7)].

7 DRUG INTERACTIONS

Granisetron does not induce or inhibit the cytochrome P-450 drug-metabolizing enzyme system in vitro. There have been no definitive drug-drug interaction studies to examine pharmacokinetic or pharmacodynamic interaction with other drugs; however, in humans, Granisetron Hydrochloride Injection has been safely administered with drugs representing benzodiazepines, neuroleptics and anti-ulcer medications commonly prescribed with antiemetic treatments. Granisetron Hydrochloride Injection also does not appear to interact with emetogenic cancer chemotherapies. Because granisetron is metabolized by hepatic cytochrome P-450 drug-metabolizing enzymes, inducers or inhibitors of these enzymes may change the clearance and, hence, the half-life of granisetron. No specific interaction studies have been conducted in anesthetized patients. In addition, the activity of the cytochrome P-450 subfamily 3A4 (involved in the metabolism of some of the main narcotic analgesic agents) is not modified by granisetron hydrochloride in vitro.

In in vitro human microsomal studies, ketoconazole inhibited ring oxidation of granisetron hydrochloride. However, the clinical significance of in vivo pharmacokinetic interactions with ketoconazole is not known. In a human pharmacokinetic study, hepatic enzyme induction with phenobarbital resulted in a 25% increase in total plasma clearance of intravenous granisetron hydrochloride. The clinical significance of this change is not known.

QT prolongation has been reported with granisetron hydrochloride. Use of granisetron hydrochloride in patients concurrently treated with drugs known to prolong the QT interval and/or are arrhythmogenic may result in clinical consequences.

Serotonin syndrome (including altered mental status, autonomic instability, and neuromuscular symptoms) has been described following the concomitant use of 5-HT3 receptor antagonists and other serotonergic drugs, including selective serotonin reuptake inhibitors (SSRIs) and serotonin and noradrenaline reuptake inhibitors (SNRIs) [see Warnings and Precautions (5.5)].

8 USE IN SPECIFIC POPULATIONS

8.1 Pregnancy

Teratogenic Effects
Pregnancy Category B
Reproduction studies have been performed in pregnant rats at intravenous doses up to 9 mg/kg/day (54 mg/m^2/day, 146 times the recommended human dose based on body surface area) and pregnant rabbits at intravenous doses up to 3 mg/kg/day (35.4 mg/m^2/day, 96 times the recommended human dose based on body surface area) and have revealed no evidence of impaired fertility or harm to the fetus due to granisetron. There are, however, no adequate and well-controlled studies in pregnant women. Because animal reproduction studies are not always predictive of human response, this drug should be used during pregnancy only if clearly needed.

Benzyl alcohol may cross the placenta. Granisetron Hydrochloride Injection 1 mg/mL is preserved with benzyl alcohol and should be used in pregnancy only if the benefit outweighs the potential risk.

8.3 Nursing Mothers

It is not known whether granisetron is excreted in human milk. Because many drugs are excreted in human milk, caution should be exercised when Granisetron Hydrochloride Injection is administered to a nursing woman.

8.4 Pediatric Use

Benzyl alcohol, a component of Granisetron Hydrochloride Injection 1 mg/mL, has been associated with serious adverse reactions and death, particularly in neonates [see Warnings and Precautions (5.4)].

Chemotherapy-Induced Nausea and Vomiting
[See Dosage and Administration (2)] for use in chemotherapy-induced nausea and vomiting in pediatric patients 2 to 16 years of age. Safety and effectiveness in pediatric patients under 2 years of age have not been established.

Postoperative Nausea and Vomiting
Safety and efficacy have not been established in pediatric patients for the prevention of postoperative nausea and vomiting (PONV). Granisetron has been evaluated in a pediatric patient clinical trial for use in the prevention of PONV. Due to the lack of efficacy and the QT prolongation observed in this trial, use of granisetron for the prevention of PONV in children is not recommended. The trial was a prospective, multicenter, randomized, double-blind, parallel-group trial that evaluated 157 children aged 2 to 16 years who were undergoing elective surgery for tonsillectomy or adenotonsillectomy. The purpose of the trial was to assess two dose levels (20 mcg/kg and 40 mcg/kg) of intravenous granisetron in the prevention of PONV. There was no active comparator or placebo. The primary endpoint was total control of nausea and vomiting (defined as no nausea, vomiting/retching, or use of rescue medication) in the 24 hours following surgery. Efficacy was not established due to lack of a dose response.

The trial also included standard 12 lead ECGs performed pre-dose and after the induction of anesthesia. ECGs were repeated at the end of surgery after the administration of granisetron and just prior to reversal of anesthesia. QT prolongation was seen at both dose levels. Five patients in this trial experienced an increase of ≥ 60 msec in QTcF. In addition, there were two patients whose QTcF was ≥ 500 msec. Interpretation of the QTcF prolongation was confounded by multiple factors, including the use of concomitant medication and the lack of either a placebo or active control. A thorough QT trial in adults has not been performed.

Other adverse events that occurred in the study included: vomiting (5 to 8%), post-procedural hemorrhage (3 to 5%), and dehydration (0 to 5%).

Pediatric patients under 2 years of age have not been studied.

8.5 Geriatric Use

During chemotherapy clinical trials, 713 patients 65 years of age or older received Granisetron Hydrochloride Injection. The safety and effectiveness were similar in patients of various ages.

10 OVERDOSAGE

There is no specific antidote for Granisetron Hydrochloride Injection overdosage. In case of overdosage, symptomatic treatment should be given. Overdosage of up to 38.5 mg of granisetron hydrochloride injection has been reported without symptoms or only the occurrence of a slight headache.

11 DESCRIPTION

Granisetron Hydrochloride Injection, USP is a serotonin-3 (5-HT3) receptor antagonist. Chemically it is endo-N-(9-methyl-9-azabicyclo [3.3.1] non-3-yl)-1-methyl-1H-indazole-3-carboxamide hydrochloride with a molecular weight of 348.9 (312.4 free base). Its empirical formula is C18H24N4O•HCl, while its chemical structure is:

Granisetron hydrochloride is a white to off-white solid that is readily soluble in water and normal saline at 20°C. Granisetron Hydrochloride Injection, USP is a clear, colorless, sterile, nonpyrogenic, aqueous solution for intravenous administration.

Granisetron Hydrochloride Injection, USP 1 mg/mL is available in 1 mL single dose and 4 mL multiple dose vials.

1 mg/mL: Each mL contains 1.12 mg granisetron hydrochloride equivalent to granisetron, 1 mg; sodium chloride, 9 mg; citric acid anhydrous, 2 mg; and benzyl alcohol, 10 mg, as a preservative. The solution’s pH ranges from 4.0 to 6.0; pH adjusted with sodium hydroxide/hydrochloric acid.

12 CLINICAL PHARMACOLOGY

12.1 Mechanism of Action

Granisetron is a selective 5-hydroxytryptamine3 (5-HT3) receptor antagonist with little or no affinity for other serotonin receptors, including 5-HT1; 5-HT1A; 5-HT1B/C; 5-HT2; for alpha1-, alpha2- or beta-adrenoreceptors; for dopamine-D2; or for histamine-H1; benzodiazepine; picrotoxin or opioid receptors.

Serotonin receptors of the 5-HT3 type are located peripherally on vagal nerve terminals and centrally in the chemoreceptor trigger zone of the area postrema. During chemotherapy-induced vomiting, mucosal enterochromaffin cells release serotonin, which stimulates 5-HT3 receptors. This evokes vagal afferent discharge and may induce vomiting. Animal studies demonstrate that, in binding to 5-HT3 receptors, granisetron blocks serotonin stimulation and subsequent vomiting after emetogenic stimuli such as cisplatin. In the ferret animal model, a single granisetron injection prevented vomiting due to high-dose cisplatin or arrested vomiting within 5 to 30 seconds.

In most human studies, granisetron has had little effect on blood pressure, heart rate or ECG. No evidence of an effect on plasma prolactin or aldosterone concentrations has been found in other studies.

Granisetron Hydrochloride Injection exhibited no effect on oro-cecal transit time in normal volunteers given a single intravenous infusion of 50 mcg/kg or 200 mcg/kg. Single and multiple oral doses slowed colonic transit in normal volunteers.

12.3 Pharmacokinetics

Chemotherapy-Induced Nausea and Vomiting
In adult cancer patients undergoing chemotherapy and in volunteers, mean pharmacokinetic data obtained from an infusion of a single 40 mcg/kg dose of Granisetron Hydrochloride Injection are shown in Table 2.

Table 2. Pharmacokinetic Parameters in Adult Cancer Patients Undergoing Chemotherapy and in Volunteers, Following a Single Intravenous 40 mcg/kg Dose of Granisetron Hydrochloride Injection
 | Peak Plasma Concentration (ng/mL) | Terminal Phase Plasma Half-Life (h) | Total Clearance (L/h/kg) | Volume of Distribution (L/kg)
Cancer Patients
Mean | 63.8 [5-minute infusion.] | 8.95 | 0.38 | 3.07
Range | 18.0 to 176 | 0.90 to 31.1 | 0.14 to 1.54 | 0.85 to 10.4
Volunteers
21 to 42 years
Mean | 64.3 [3-minute infusion.] | 4.91 | 0.79 | 3.04
Range | 11.2 to 182 | 0.88 to 15.2 | 0.20 to 2.56 | 1.68 to 6.13
65 to 81 years
Mean | 57.0 | 7.69 | 0.44 | 3.97
Range | 14.6 to 153 | 2.65 to 17.7 | 0.17 to 1.06 | 1.75 to 7.01

Distribution
Plasma protein binding is approximately 65% and granisetron distributes freely between plasma and red blood cells.

Metabolism
Granisetron metabolism involves N-demethylation and aromatic ring oxidation followed by conjugation. In vitro liver microsomal studies show that granisetron’s major route of metabolism is inhibited by ketoconazole, suggestive of metabolism mediated by the cytochrome P-450 3A subfamily. Animal studies suggest that some of the metabolites may also have 5-HT3 receptor antagonist activity.

Elimination
Clearance is predominantly by hepatic metabolism. In normal volunteers, approximately 12% of the administered dose is eliminated unchanged in the urine in 48 hours. The remainder of the dose is excreted as metabolites, 49% in the urine, and 34% in the feces.

Subpopulations
Gender
There was high inter- and intra-subject variability noted in these studies. No difference in mean AUC was found between males and females, although males had a higher Cmax generally.

Elderly
The ranges of the pharmacokinetic parameters in elderly volunteers (mean age 71 years), given a single 40 mcg/kg intravenous dose of Granisetron Hydrochloride Injection, were generally similar to those in younger healthy volunteers; mean values were lower for clearance and longer for half-life in the elderly patients (see Table 2).

Pediatric Patients
A pharmacokinetic study in pediatric cancer patients (2 to 16 years of age), given a single 40 mcg/kg intravenous dose of Granisetron Hydrochloride Injection, showed that volume of distribution and total clearance increased with age. No relationship with age was observed for peak plasma concentration or terminal phase plasma half-life. When volume of distribution and total clearance are adjusted for body weight, the pharmacokinetics of granisetron are similar in pediatric and adult cancer patients.

Renal Failure Patients
Total clearance of granisetron was not affected in patients with severe renal failure who received a single 40 mcg/kg intravenous dose of Granisetron Hydrochloride Injection.

Hepatically Impaired Patients
A pharmacokinetic study in patients with hepatic impairment due to neoplastic liver involvement showed that total clearance was approximately halved compared to patients without hepatic impairment. Given the wide variability in pharmacokinetic parameters noted in patients, dosage adjustment in patients with hepatic functional impairment is not necessary.

13 NONCLINICAL TOXICOLOGY

13.1 Carcinogenesis, Mutagenesis, Impairment of Fertility

In a 24-month carcinogenicity study, rats were treated orally with granisetron 1, 5 or 50 mg/kg/day (6, 30 or 300 mg/m2/day). The 50 mg/kg/day dose was reduced to 25 mg/kg/day (150 mg/m2/day) during week 59 due to toxicity. For a 50 kg person of average height (1.46 m2 body surface area), these doses represent 16, 81 and 405 times the recommended clinical dose (0.37 mg/m2, iv) on a body surface area basis. There was a statistically significant increase in the incidence of hepatocellular carcinomas and adenomas in males treated with 5 mg/kg/day (30 mg/m2/day, 81 times the recommended human dose based on body surface area) and above, and in females treated with 25 mg/kg/day (150 mg/m2/day, 405 times the recommended human dose based on body surface area). No increase in liver tumors was observed at a dose of 1 mg/kg/day (6 mg/m2/day, 16 times the recommended human dose based on body surface area) in males and 5 mg/kg/day (30 mg/m2/day, 81 times the recommended human dose based on body surface area) in females. In a 12-month oral toxicity study, treatment with granisetron 100 mg/kg/day (600 mg/m2/day, 1622 times the recommended human dose based on body surface area) produced hepatocellular adenomas in male and female rats while no such tumors were found in the control rats. A 24-month mouse carcinogenicity study of granisetron did not show a statistically significant increase in tumor incidence, but the study was not conclusive.

Because of the tumor findings in rat studies, Granisetron Hydrochloride Injection should be prescribed only at the dose and for the indication recommended [see Indications and Usage (1) and Dosage and Administration (2)].

Granisetron was not mutagenic in an in vitro Ames test and mouse lymphoma cell forward mutation assay, and in vivo mouse micronucleus test and in vitro and ex vivo rat hepatocyte UDS assays. It, however, produced a significant increase in UDS in HeLa cells in vitro and a significant increased incidence of cells with polyploidy in an in vitro human lymphocyte chromosomal aberration test.

Granisetron at subcutaneous doses up to 6 mg/kg/day (36 mg/m2/day, 97 times the recommended human dose based on body surface area) was found to have no effect on fertility and reproductive performance of male and female rats.

14 CLINICAL STUDIES

14.1 Chemotherapy-Induced Nausea and Vomiting

Single-Day Chemotherapy
Cisplatin-Based Chemotherapy
In a double-blind, placebo-controlled study in 28 cancer patients, Granisetron Hydrochloride Injection, administered as a single intravenous infusion of 40 mcg/kg, was significantly more effective than placebo in preventing nausea and vomiting induced by cisplatin chemotherapy (see Table 3).

Table 3. Prevention of Chemotherapy-Induced Nausea and Vomiting - Single-Day Cisplatin Therapy [Cisplatin administration began within 10 minutes of Granisetron Hydrochloride Injection infusion and continued for 1.5 to 3.0 hours. Mean cisplatin dose was 86 mg/m^2 in the Granisetron Hydrochloride Injection group and 80 mg/m^2 in the placebo group.]
 | Granisetron Hydrochloride Injection | Placebo | P-Value
Number of Patients | 14 | 14
Response Over 24 Hours
Complete Response [No vomiting and no moderate or severe nausea.] | 93% | 7% | <0.001
No Vomiting | 93% | 14% | <0.001
No More Than Mild Nausea | 93% | 7% | <0.001

Granisetron Hydrochloride Injection was also evaluated in a randomized dose response study of cancer patients receiving cisplatin ≥75 mg/m^2. Additional chemotherapeutic agents included: anthracyclines, carboplatin, cytostatic antibiotics, folic acid derivatives, methylhydrazine, nitrogen mustard analogs, podophyllotoxin derivatives, pyrimidine analogs, and vinca alkaloids. Granisetron Hydrochloride Injection doses of 10 and 40 mcg/kg were superior to 2 mcg/kg in preventing cisplatin-induced nausea and vomiting, but 40 mcg/kg was not significantly superior to 10 mcg/kg (see Table 4).

Table 4. Prevention of Chemotherapy-Induced Nausea and Vomiting — Single-Day High-Dose Cisplatin Therapy [Cisplatin administration began within 10 minutes of Granisetron Hydrochloride Injection infusion and continued for 2.6 hours (mean). Mean cisplatin doses were 96 to 99 mg/m^2.]
 | Granisetron Hydrochloride Injection (mcg/kg) |  |  | P-Value (vs. 2 mcg/kg)
 | 2 | 10 | 40 | 10 | 40
Number of Patients | 52 | 52 | 53
Response Over 24 Hours
Complete Response [No vomiting and no moderate or severe nausea.] | 31% | 62% | 68% | <0.002 | <0.001
No Vomiting | 38% | 65% | 74% | <0.001 | <0.001
No More Than Mild Nausea | 58% | 75% | 79% | NS | 0.007

Granisetron Hydrochloride Injection was also evaluated in a double-blind, randomized dose response study of 353 patients stratified for high (≥80 to 120 mg/m^2) or low (50 to 79 mg/m^2) cisplatin dose. Response rates of patients for both cisplatin strata are given in Table 5.

Table 5. Prevention of Chemotherapy-Induced Nausea and Vomiting — Single-Day High-Dose and Low-Dose Cisplatin Therapy [Cisplatin administration began within 10 minutes of Granisetron Hydrochloride Injection infusion and continued for 2 hours (mean). Mean cisplatin doses were 64 and 98 mg/m^2 for low and high strata.]
 | Granisetron Hydrochloride Injection (mcg/kg) |  |  |  | P-Value (vs. 5 mcg/kg)
 | 5 | 10 | 20 | 40 | 10 | 20 | 40
High-Dose Cisplatin
Number of Patients | 40 | 49 | 48 | 47
Response Over 24 Hours
Complete Response [No vomiting and no use of rescue antiemetic.] | 18% | 41% | 40% | 47% | 0.018 | 0.025 | 0.004
No Vomiting | 28% | 47% | 44% | 53% | NS | NS | 0.016
No Nausea | 15% | 35% | 38% | 43% | 0.036 | 0.019 | 0.005
Low-Dose Cisplatin
Number of Patients | 42 | 41 | 40 | 46
Response Over 24 Hours
Complete Response | 29% | 56% | 58% | 41% | 0.012 | 0.009 | NS
No Vomiting | 36% | 63% | 65% | 43% | 0.012 | 0.008 | NS
No Nausea | 29% | 56% | 38% | 33% | 0.012 | NS | NS

For both the low and high cisplatin strata, the 10, 20, and 40 mcg/kg doses were more effective than the 5 mcg/kg dose in preventing nausea and vomiting within 24 hours of chemotherapy administration. The 10 mcg/kg dose was at least as effective as the higher doses.

Moderately Emetogenic Chemotherapy
Granisetron Hydrochloride Injection, 40 mcg/kg, was compared with the combination of chlorpromazine (50 to 200 mg/24 hours) and dexamethasone (12 mg) in patients treated with moderately emetogenic chemotherapy, including primarily carboplatin >300 mg/m2, cisplatin 20 to 50 mg/m2 and cyclophosphamide >600 mg/m2. Granisetron Hydrochloride Injection was superior to the chlorpromazine regimen in preventing nausea and vomiting (see Table 6).

Table 6. Prevention of Chemotherapy-Induced Nausea and Vomiting — Single-Day Moderately Emetogenic Chemotherapy
 | Granisetron Hydrochloride Injection | Chlorpromazine [Patients also received dexamethasone, 12 mg.] | P-Value
Number of Patients | 133 | 133
Response Over 24 Hours
Complete Response [No vomiting and no moderate or severe nausea.] | 68% | 47% | <0.001
No Vomiting | 73% | 53% | <0.001
No More Than Mild Nausea | 77% | 59% | <0.001

In other studies of moderately emetogenic chemotherapy, no significant difference in efficacy was found between granisetron hydrochloride doses of 40 mcg/kg and 160 mcg/kg.

Repeat-Cycle Chemotherapy
In an uncontrolled trial, 512 cancer patients received Granisetron Hydrochloride Injection, 40 mcg/kg, prophylactically, for two cycles of chemotherapy, 224 patients received it for at least four cycles, and 108 patients received it for at least six cycles. Granisetron Hydrochloride Injection efficacy remained relatively constant over the first six repeat cycles, with complete response rates (no vomiting and no moderate or severe nausea in 24 hours) of 60% to 69%. No patients were studied for more than 15 cycles.

Pediatric Studies
A randomized double-blind study evaluated the 24-hour response of 80 pediatric cancer patients (age 2 to 16 years) to Granisetron Hydrochloride Injection 10, 20 or 40 mcg/kg. Patients were treated with cisplatin ≥60 mg/m^2, cytarabine ≥3 g/m^2, cyclophosphamide ≥1 g/m^2 or nitrogen mustard ≥6 mg/m^2 (see Table 7).

Table 7. Prevention of Chemotherapy-Induced Nausea and Vomiting in Pediatric Patients
 | Granisetron Hydrochloride Injection Dose (mcg/kg)
 | 10 | 20 | 40
Number of Patients | 29 | 26 | 25
Median Number of Vomiting Episodes | 2 | 3 | 1
Complete Response Over 24 Hours [No vomiting and no moderate or severe nausea.] | 21% | 31% | 32%

A second pediatric study compared Granisetron Hydrochloride Injection 20 mcg/kg to chlorpromazine plus dexamethasone in 88 patients treated with ifosfamide ≥3 g/m^2/day for two or three days. Granisetron Hydrochloride Injection was administered on each day of ifosfamide treatment. At 24 hours, 22% of Granisetron Hydrochloride Injection patients achieved complete response (no vomiting and no moderate or severe nausea in 24 hours) compared with 10% on the chlorpromazine regimen. The median number of vomiting episodes with Granisetron Hydrochloride Injection was 1.5; with chlorpromazine it was 7.

16 HOW SUPPLIED/STORAGE AND HANDLING

Granisetron Hydrochloride Injection, USP 1 mg/mL (free base), is supplied in 1 mL Single Dose Vials and 4 mL Multiple Dose Vials. CONTAINS BENZYL ALCOHOL.

NDC 0143-9744-10 (Carton of 10 x 1 mL Single Dose Vials)
NDC 0143-9745-10 (Carton of 10 x 4 mL Multiple Dose Vials)
NDC 0143-9745-05 (Carton of 5 x 4 mL Multiple Dose Vials)

Store single dose vials and multiple dose vials at 20° to 25°C (68° to 77°F); excursions permitted to 15° to 30°C (59° to 86°F). [See USP Controlled Room Temperature]

Discard unused portion for the single dose vials.

Once the multiple dose vial is penetrated, its contents should be used within 30 days.

Do not freeze. Protect from light. Retain in carton until time of use.

17 PATIENT COUNSELING INFORMATION

Patients should be informed that the most common adverse reactions for the indication of chemotherapy induced nausea and vomiting are headache and constipation (see Table 1).

Patients should be advised of the risk of allergic reactions if they have a prior allergic reaction to a class of antiemetics known as 5-HT3 receptor antagonists.

Electrocardiogram changes (QT prolongation) have been reported with the use of granisetron hydrochloide. Patients should be cautioned about the use of this drug if they have heart problems or take medications for heart problems.

Patients should be informed that Granisetron Hydrochloride Injection (1 mg/mL) contains benzyl alcohol and may cause serious side effects in newborns.

Advise patients of the possibility of serotonin syndrome with concomitant use of granisetron and another serotonergic agent such as medications to treat depression and migraines. Advise patients to seek immediate medical attention if the following symptoms occur: changes in mental status, autonomic instability, neuromuscular symptoms with or without gastrointestinal symptoms.

Manufactured by:
HIKMA FARMACÊUTICA (PORTUGAL), S.A.
Estrada do Rio da Mó, nº 8, 8A e 8B - Fervença,
2705 – 906 Terrugem SNT
PORTUGAL

Distributed by:
Hikma Pharmaceuticals USA Inc.
Berkeley Heights, NJ 07922

Revised: August 2020

PIN225-WES/7

PRINCIPAL DISPLAY PANEL

NDC 0143-9744-01 Rx only
Granisetron
Hydrochloride
Injection, USP
1 mg/mL
For Intravenous Use ONLY
1 mL Single Dose Vial

NDC 0143-9744-10 Rx only

Granisetron

Hydrochloride

Injection, USP

1 mg/mL*

For Intravenous use ONLY

10 x 1 mL Single Dose Vials

PRINCIPAL DISPLAY PANEL

NDC 0143-9745-01 Rx only
Granisetron
Hydrochloride
Injection, USP
4 mg per 4 mL
(1 mg/mL)
For Intravenous Use ONLY
4 mL Multiple Dose Vial

NDC 0143-9745-05 Rx only
Granisetron
Hydrochloride
Injection, USP
4 mg per 4 mL
(1 mg/mL*)
For Intravenous Use ONLY
5 x 4 mL Multiple Dose Vials

NDC 0143-9745-10 Rx only
Granisetron
Hydrochloride
Injection, USP
4 mg per 4 mL
(1 mg/mL*)
For Intravenous Use ONLY
10 x 4 mL Multiple Dose Vials